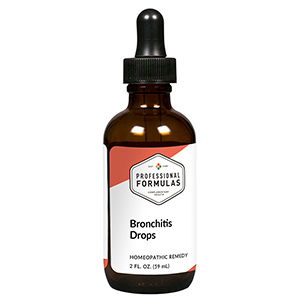 DRUG LABEL: Bronchitis Drops
NDC: 63083-2170 | Form: LIQUID
Manufacturer: Professional Complementary Health Formulas
Category: homeopathic | Type: HUMAN OTC DRUG LABEL
Date: 20190815

ACTIVE INGREDIENTS: CETRARIA ISLANDICA WHOLE 1 [hp_X]/59 mL; EUCALYPTUS GLOBULUS LEAF 1 [hp_X]/59 mL; PIMPINELLA SAXIFRAGA ROOT 2 [hp_X]/59 mL; IPECAC 4 [hp_X]/59 mL; ANTIMONY POTASSIUM TARTRATE 6 [hp_X]/59 mL
INACTIVE INGREDIENTS: ALCOHOL; WATER

C170

ACTIVE INGREDIENTS

Cetraria islandica 1X
Eucalyptus globulus 1X
Pimpinella saxifraga 2X
Ipecacuanha 4X
Antimonium tartaricum 6X

QUESTIONS

Professional Formulas

PO Box 2034 Lake Oswego, OR 97035

INDICATIONS

For the temporary relief of coughing and irritation, tenderness, or mild pain in the nose or throat.*

PURPOSE

*Claims based on traditional homeopathic practice, not accepted medical evidence. Not FDA evaluated.

WARNINGS

If symptoms do not improve or are accompanied by a fever, consult a doctor. Keep out of the reach of children. In case of overdose, get medical help or contact a poison control center right away. If pregnant or breastfeeding, ask a healthcare professional before use.

Keep out of the reach of children.

PREGNANCY OR BREAST FEEDING

If pregnant or breastfeeding, ask a healthcare professional before use.

DIRECTIONS

Place drops under tongue 30 minutes before/after meals. Adults and children 12 years and over: Take 10 drops up to 3 times per day for up to 6 weeks. For immediate onset of symptoms, take 10 to 15 drops every 15 minutes up to 3 hours. For less severe symptoms, take 10-15 drops hourly up to 8 hours. Consult a physician for use in children under 12 years of age.

OTHER INFORMATION

Tamper resistant. If seal is broken, do not use. After opening, close container tightly and store at room temperature away from heat.

INACTIVE INGREDIENTS

20% ethanol, purified water.

LABEL

Est 1985

Professional Formulas

Complementary Health

Bronchitis Drops

Homeopathic Remedy

2 FL. OZ. (59 mL)